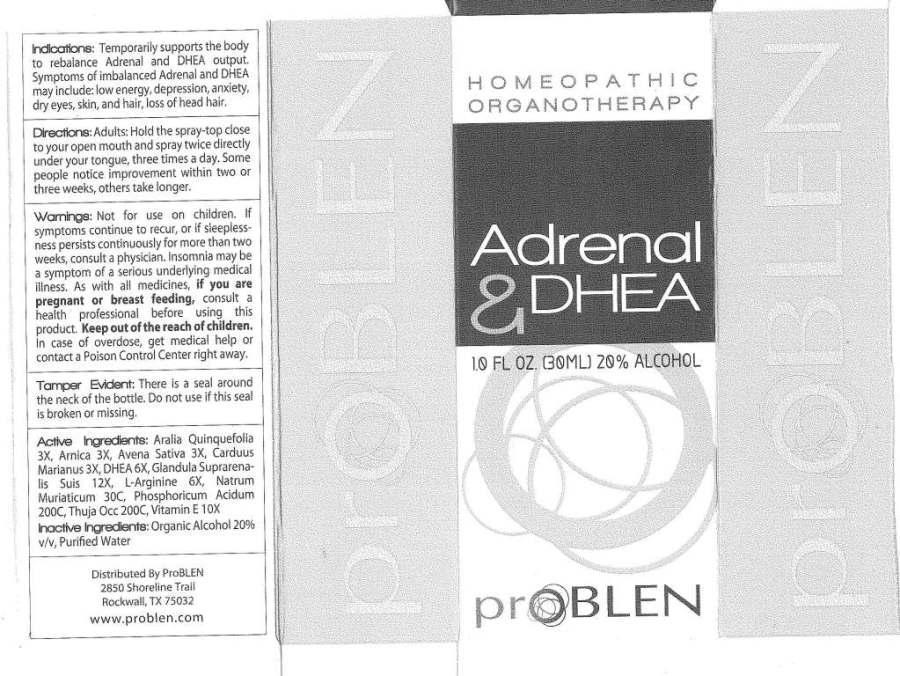 DRUG LABEL: Adrenal and DHEA
NDC: 43853-0008 | Form: LIQUID
Manufacturer: ProBLEN
Category: homeopathic | Type: HUMAN OTC DRUG LABEL
Date: 20130423

ACTIVE INGREDIENTS: AMERICAN GINSENG 3 [hp_X]/1 mL; ARNICA MONTANA 3 [hp_X]/1 mL; AVENA SATIVA FLOWERING TOP 3 [hp_X]/1 mL; SILYBUM MARIANUM SEED 3 [hp_X]/1 mL; PRASTERONE 6 [hp_X]/1 mL; SUS SCROFA ADRENAL GLAND 12 [hp_X]/1 mL; ARGININE 6 [hp_X]/1 mL; SODIUM CHLORIDE 30 [hp_X]/1 mL; PHOSPHORIC ACID 200 [hp_C]/1 mL; THUJA OCCIDENTALIS LEAF 200 [hp_C]/1 mL; .ALPHA.-TOCOPHEROL 10 [hp_X]/1 mL
INACTIVE INGREDIENTS: WATER; ALCOHOL

Drug Facts

ACTIVE INGREDIENTS

Aralia Quinquefolia 3X, Arnica Montana 3X, Avena Sativa 3X, Carduus Marianus 3X, DHEA 6X, Glandula Suprarenalis Suis 12X, L-Arginine 6X, Natrum Muriaticum 30C, Phosphoricum Acidum 200C, Thuja Occidentalis 200C, Vitamin E 10X

INDICATIONS

Temporarily supports the body to rebalance Adrenal and DHEA output. Symptoms of imbalanced Adrenal and DHEA may include: low energy, depression, anxiety, dry eyes, skin, and hair, loss of head hair.

WARNINGS

Not for use on children. If symptoms continue to recur, or if sleeplessness persists continuously for more than two weeks, consult a physician. Insomnia may be a symptom of a serious underlying medical illness. As with all medicines, if you are pregnant or breast feeding, consult a health professional before using this product. Keep out of the reach of children. In case of overdose, get medical help or contact a Poison Control Center right away.

There is a seal around the neck of the bottle. Do not use if this seal is broken or missing.

DIRECTIONS

Adults: Hold the spray-top close to your open mouth and spray twice directly under your tongue, three times a day. Some people notice improvement within two or three weeks, others take longer.

INACTIVE INGREDIENTS

Purified Water, Organic Ethanol 20%

KEEP OUT OF REACH OF CHILDREN

In case of overdose, get medical help or contact a Poison Control Center right away.

INDICATIONS AND USAGE

Temporarily supports the body to rebalance Adrenal and DHEA output. Symptoms of imbalanced Adrenal and DHEA may include: low energy, depression, anxiety, dry eyes, skin, and hair, loss of head hair.

QUESTIONS

Distributed By ProBLEN

2850 Shoreline Trail

Rockwall, TX 75032

www.problen.com

PACKAGE LABEL

HOMEOPATHIC

ORGANOTHERAPY

Adrenal and

DHEA

1.0 FL OZ. (30 ML)

proBLEN